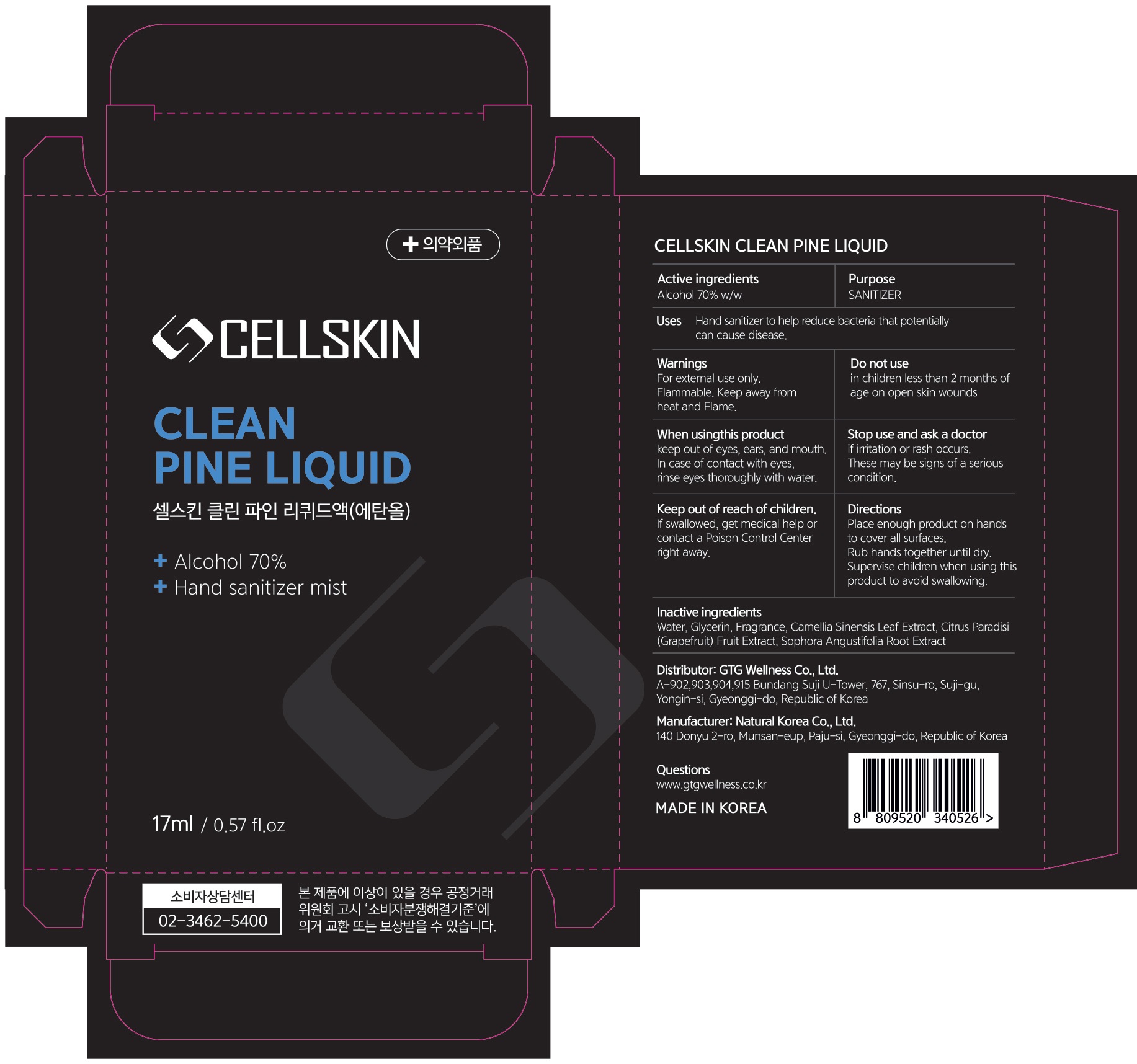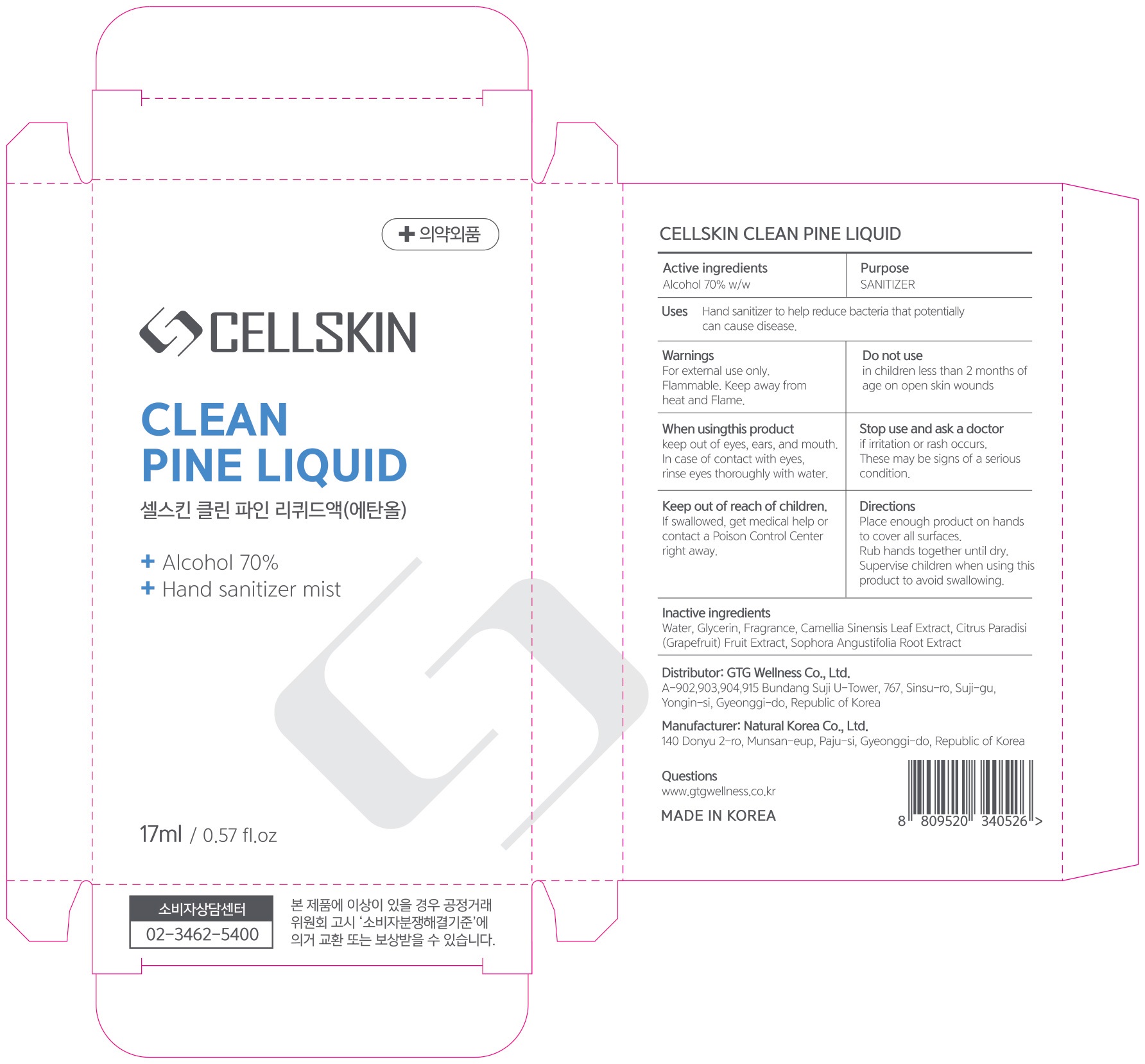 DRUG LABEL: CELLSKIN CLEAN PINE
NDC: 71080-0021 | Form: LIQUID
Manufacturer: GTG Wellness Co., Ltd.
Category: otc | Type: HUMAN OTC DRUG LABEL
Date: 20201210

ACTIVE INGREDIENTS: ALCOHOL 11.9 g/17 mL
INACTIVE INGREDIENTS: Water; Glycerin; GREEN TEA LEAF; GRAPEFRUIT; SOPHORA FLAVESCENS ROOT

ACTIVE INGREDIENT

Alcohol 70% w/w

INACTIVE INGREDIENTS

Water, Glycerin, Fragrance, Camellia Sinensis Leaf Extract, Citrus Paradisi (Grapefruit) Fruit Extract, Sophora Angustifolia Root Extract

PURPOSE

SANITIZER

WARNINGS

For external use only. Flammable. Keep away from heat and Flame.
--------------------------------------------------------------------------------------------------------
Do not use
• in children less than 2 months of age
• on open skin wounds

--------------------------------------------------------------------------------------------------------
When using this product keep out of eyes, ears, and mouth. In case of contact with eyes, rinse eyes thoroughly with water.
--------------------------------------------------------------------------------------------------------
Stop use and ask a doctor if irritation or rash occurs. These may be signs of a serious condition.
--------------------------------------------------------------------------------------------------------
Keep out of reach of children. If swallowed, get medical help or contact a Poison Control Center right away.

KEEP OUT OF REACH OF CHILDREN

If swallowed, get medical help or contact a Poison Control Center right away.

Uses

■ Hand sanitizer to help reduce bacteria that potentially can cause disease.

Directions

■ Place enough product on hands to cover all surfaces.
■ Rub hands together until dry.
■ Supervise children when using this product to avoid swallowing.

QUESTIONS

www.gtgwellness.co.kr